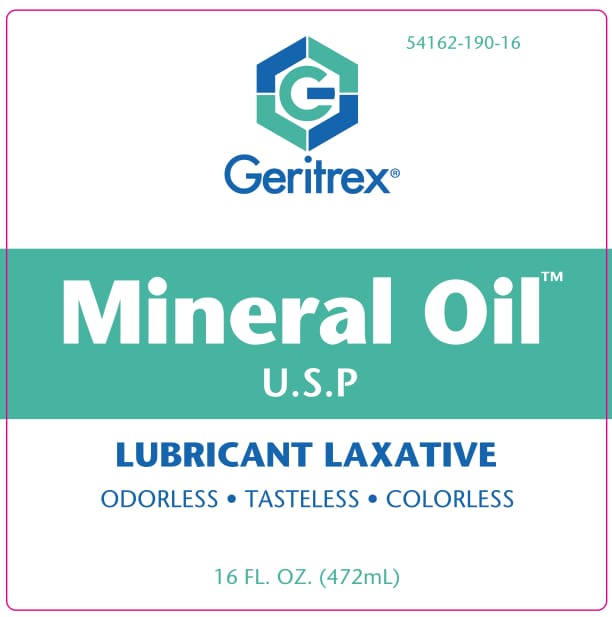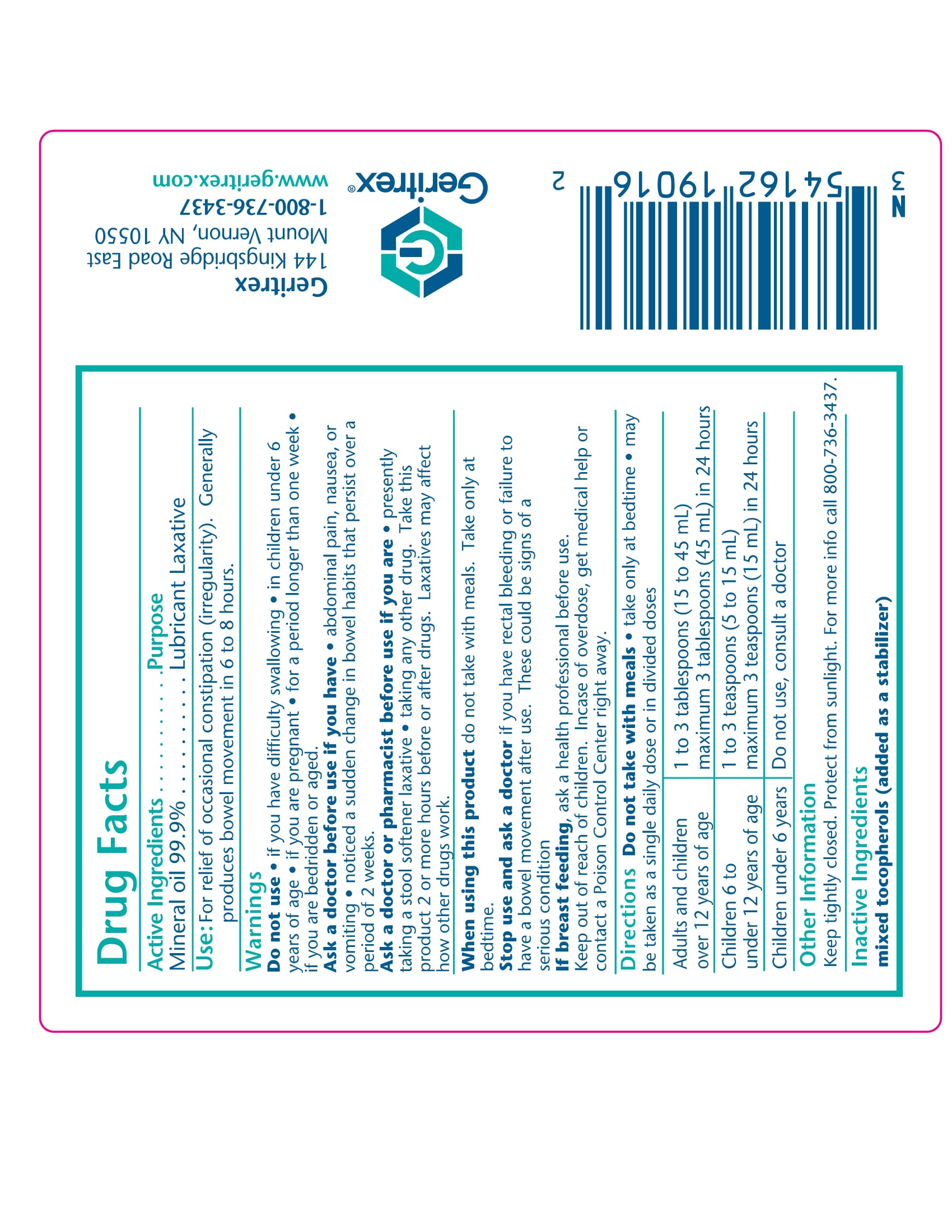 DRUG LABEL: Mineral oil Light, N.F
NDC: 54162-185 | Form: OIL
Manufacturer: GERITREX LLC
Category: otc | Type: HUMAN OTC DRUG LABEL
Date: 20170828

ACTIVE INGREDIENTS: MINERAL OIL 471.99 g/472 mL
INACTIVE INGREDIENTS: .ALPHA.-TOCOPHEROL, DL- 0.00472 g/472 mL

Mineral Oil

Active Ingredient:

Mineral Oil 100%

Use:

Helps treat and prevent diaper rash, protects chafted skin and seals out wetness.

INDICATIONS AND USAGE

Protects skin.

Keep out of reach of children

WARNINGS

Caution: For External Use Only

In case of accidental ingestion seek professional assistance or contact a Poison Control Center immediately. Avoid contact with eyes. In case of accidental eye contactl flush eyes gently with water for 15 minutes. Obtain medical attention if irritation persists. If diaper rash worsens or does not improve consult a physician

DOSAGE AND ADMINISTRATION

Clean area thoroughly and allow to dry. Apply mineral oil liberally and as often as needed. Protects the skin against wetness.

INACTIVE INGREDIENT

Contains:

dl-alpha-tocopherol as preservative. Keep tightly closed and protect from direct sunlight.

STORAGE AND HANDLING

Store at room temperature 15-30°C (59-86°F)